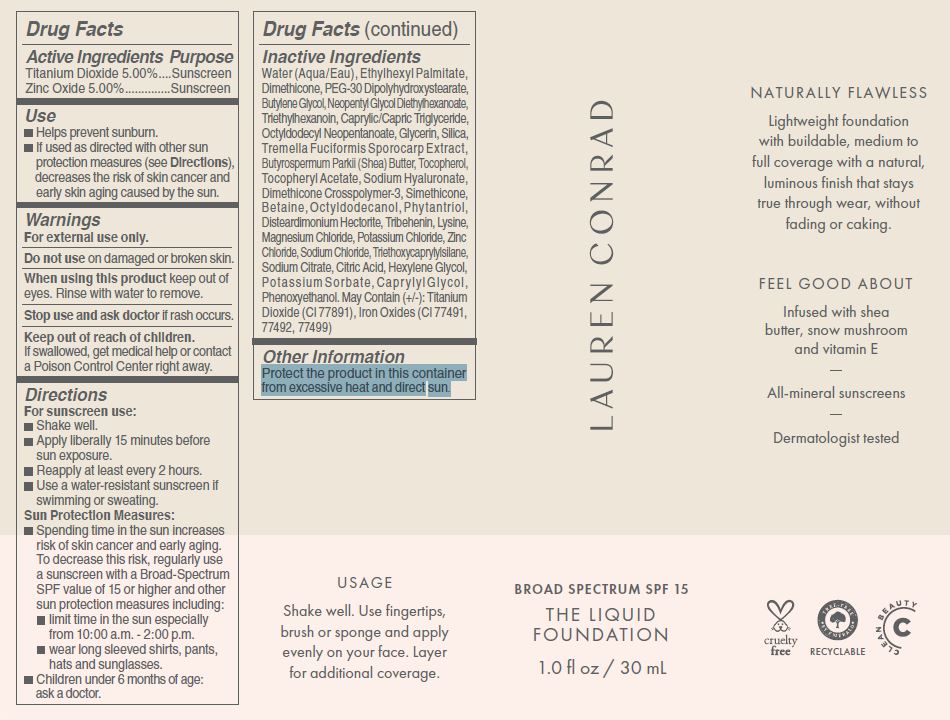 DRUG LABEL: LAUREN CONRAD - THE LIQUID FOUNDATION
NDC: 80261-101 | Form: CREAM
Manufacturer: Lauren Conrad Beauty Co.
Category: otc | Type: HUMAN OTC DRUG LABEL
Date: 20200831

ACTIVE INGREDIENTS: TITANIUM DIOXIDE 5 g/100 mL; ZINC OXIDE 5 g/100 mL
INACTIVE INGREDIENTS: WATER; Ethylhexyl Palmitate; Dimethicone; PEG-30 Dipolyhydroxystearate; Butylene Glycol; Neopentyl Glycol Diethylhexanoate; Triethylhexanoin; MEDIUM-CHAIN TRIGLYCERIDES; Octyldodecyl Neopentanoate; Glycerin; SILICON DIOXIDE; TREMELLA FUCIFORMIS FRUITING BODY; SHEA BUTTER; TOCOPHEROL; .ALPHA.-TOCOPHEROL ACETATE; HYALURONATE SODIUM; DIMETHICONE CROSSPOLYMER (450000 MPA.S AT 12% IN CYCLOPENTASILOXANE); BETAINE; OCTYLDODECANOL; PHYTANTRIOL; DISTEARDIMONIUM HECTORITE; TRIBEHENIN; LYSINE; MAGNESIUM CHLORIDE; POTASSIUM CHLORIDE; ZINC CHLORIDE; SODIUM CHLORIDE; TRIETHOXYCAPRYLYLSILANE; SODIUM CITRATE; ANHYDROUS CITRIC ACID; HEXYLENE GLYCOL; POTASSIUM SORBATE; CAPRYLYL GLYCOL; PHENOXYETHANOL; FERRIC OXIDE RED

LAUREN CONRAD - THE LIQUID FOUNDATION (SPF 15)

ACTIVE INGREDIENTS

Titanium Dioxide 5.00%

Zinc Oxide 5.00%

Purpose

Sunscreen

PURPOSE

SUNSCREEN

USES

- Helps prevent sunburn.
- If used as directed with other sun protection measures (see Directions), decreases the risk of skin cancer and early skin aging caused by the sun.

WARNINGS

For external use only.

Do not use on damaged or broken skin.

When using this product keep out of eyes. Rinse with water to remove.

Stop use and ask doctor if rash occurs.

Keep out of reach of children. If product is swallowed, get medical help or contact a Poison Control Center right away.

Keep out of reach of children. If swallowed, get medical help or contact a Poison Control Center right away.

DIRECTIONS

For sunscreen use:

- Shake well.
- Apply liberally 15 minutes before sun exposure.
- Reapply at least every 2 hours.
- Use a water-resistant sunscreen if swimming or sweating.

Sun Protection Measures:

- Spending time in the sun increases risk of skin cancer and early aging. To decrease this risk, regularly use a sunscreen with a Broad-Spectrum SPF value of 15 or higher and other sun protection measures including:
- limit time in the sun especially from 10:00 a.m. - 2:00 p.m.
- wear long sleeved shirts, pants, hats and sunglasses.
- Children under 6 months of age: ask a doctor.

INACTIVE INGREDIENTS

Water (Aqua/Eau), Ethylhexyl Palmitate, Dimethicone, PEG-30 Dipolyhydroxystearate, Butylene Glycol, Neopentyl Glycol Diethylhexanoate, Triethylhexanoin, Caprylic/Capric Triglyceride, Octyldodecyl Neopentanoate, Glycerin, Silica, Tremella Fuciformis Sporocarp Extract, Butyrospermum Parkii (Shea) Butter, Tocopherol, Tocopheryl Acetate, Sodium Hyaluronate, Dimethicone Crosspolymer-3, Simethicone, Betaine, Octyldodecanol, Phytantriol, Disteardimonium Hectorite, Tribehenin, Lysine, Magnesium Chloride, Potassium Chloride, Zinc Chloride, Sodium Chloride, Triethoxycaprylylsilane, Sodium Citrate, Citric Acid, Hexylene Glycol, Potassium Sorbate, Capr ylyl Glycol, Phenoxyethanol. May Contain (+/-): Titanium Dioxide (CI 77891), Iron Oxides (CI 77491, 77492, 77499)

OTHER INFORMATION

Protect the product in this container from excessive heat and direct sun.